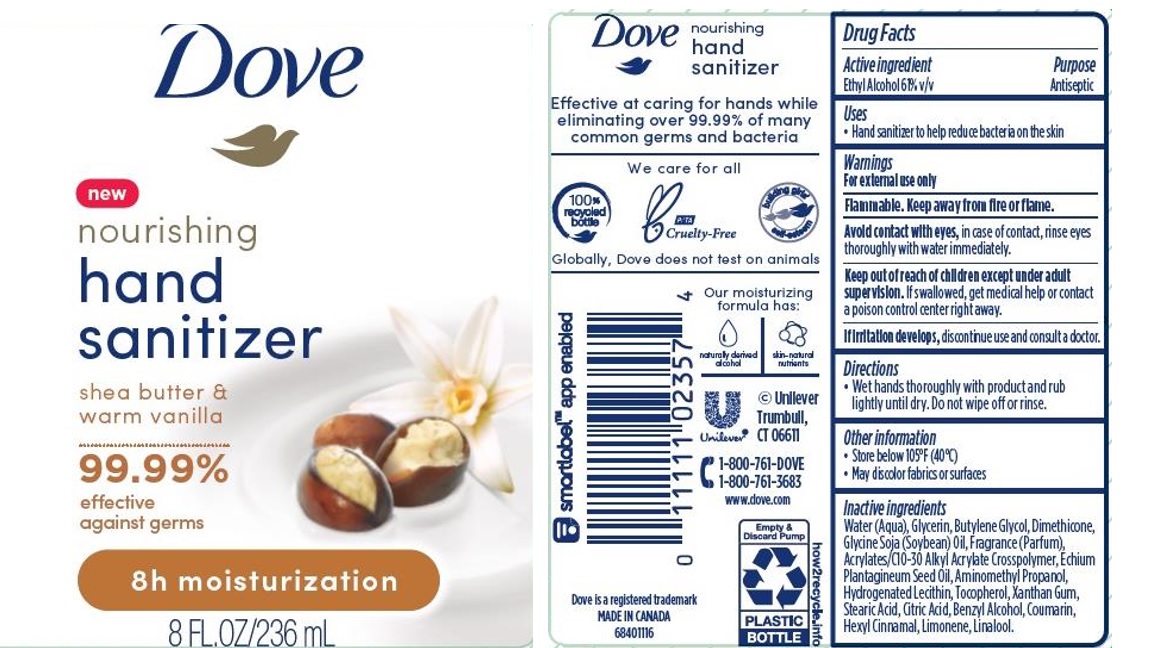 DRUG LABEL: Dove
NDC: 64942-1746 | Form: GEL
Manufacturer: Conopco Inc. d/b/a/ Unilever
Category: otc | Type: HUMAN OTC DRUG LABEL
Date: 20241024

ACTIVE INGREDIENTS: ALCOHOL 610 mg/1 mL
INACTIVE INGREDIENTS: STEARIC ACID; COUMARIN; CITRIC ACID MONOHYDRATE; BUTYLENE GLYCOL; WATER; GLYCERIN; LIMONENE, (+)-; DIMETHICONE; CARBOMER INTERPOLYMER TYPE A (ALLYL SUCROSE CROSSLINKED); ECHIUM PLANTAGINEUM SEED OIL; BENZYL ALCOHOL; AMINOMETHYLPROPANOL; HYDROGENATED SOYBEAN LECITHIN; XANTHAN GUM; TOCOPHEROL; .ALPHA.-HEXYLCINNAMALDEHYDE; SOYBEAN OIL; LINALOOL, (+/-)-

Dove Nourishing Hand Sanitizer Shea Butter & Warm Vanilla 8h Moisturization

DOVE NOURISHING HAND SANITIZER SHEA BUTTER & WARM VANILLA 8H MOISTURIZATION - Ethyl Alcohol gel

Dove Nourishing Hand Sanitizer Shea Butter & Warm Vanilla 8h Moisturization

Drug Facts

Active ingredient

Ethyl Alcohol 61%

Purpose

Antiseptic

Uses

• Hand sanitizer to help reduce bacteria on the skin

Warnings

• For external use only
• Flammable. Keep away from fire or flame
• Avoid contact with eyes, in case of contact, rinse eyes thoroughly with water immediately.
• If irritation develps, discontinue use and consult a doctor.

• Keep out of reach of children except under adult supervision.

If swallowed, get medical help or contact a poison control Center right away.

Other information

• Store below 105˚F (40˚C).
• May discolor fabrics or surfaces.

Inactive ingredients

Water (Aqua), Glycerin, Butylene Glycol, Dimethicone, Glycine Soja (Soybean) Oil, Fragrance (Parfum), Acrylates/C10-30 Alkyl Acrylate Crosspolymer, Echium Plantagineum Seed Oil, Aminomethyl Propanol, Hydrogenated Lecithin, Tocopherol, Xanthan Gum, Stearic Acid, Citric Acid, Benzyl Alcohol, Coumarin, Hexyl Cinnamal, Limonene, Linalool .

Questions?

1-800-761-3683